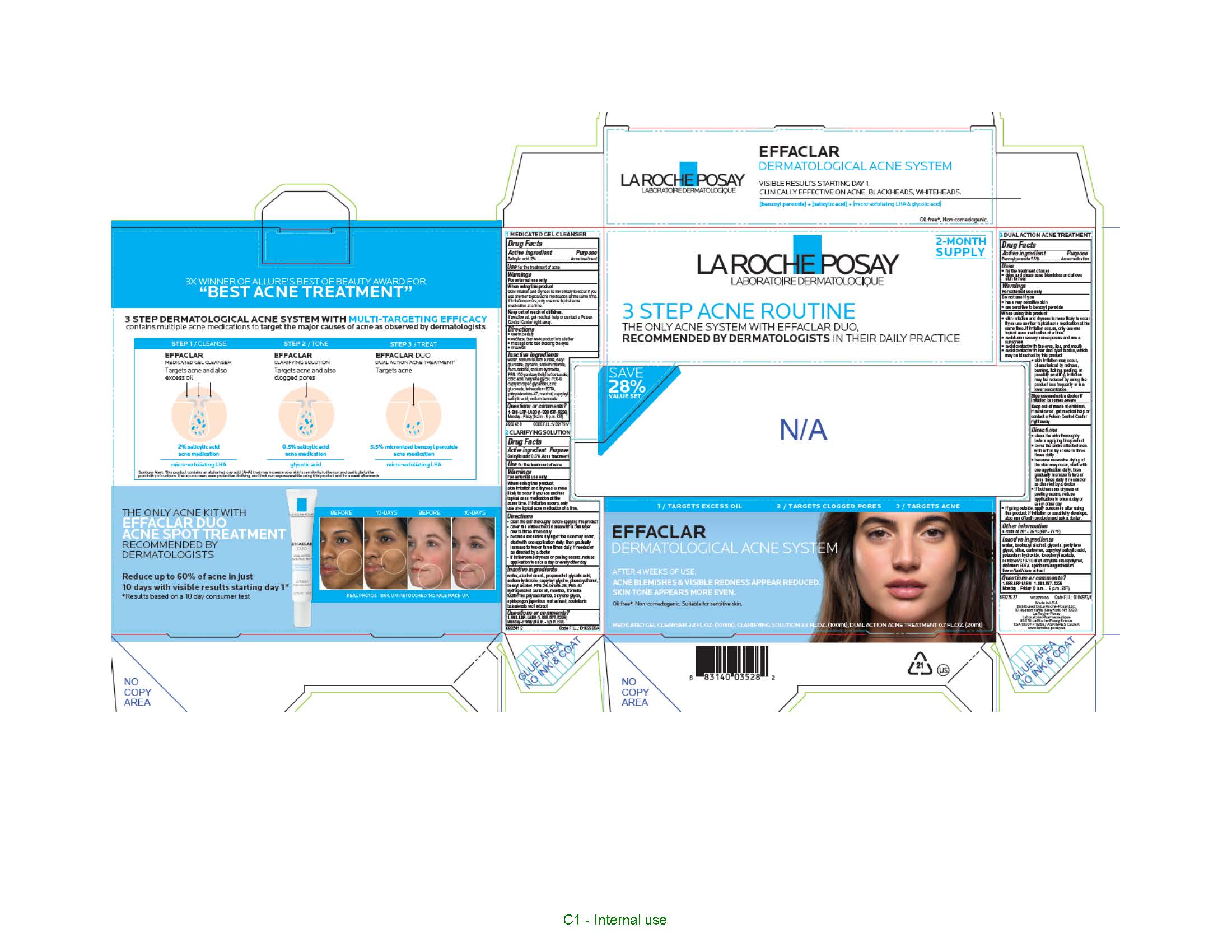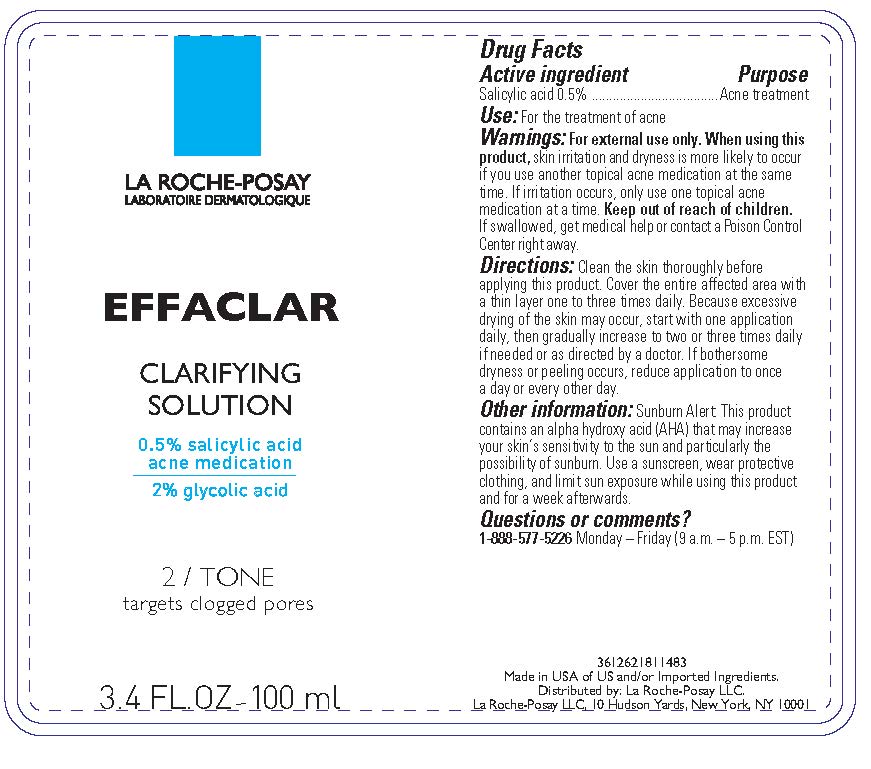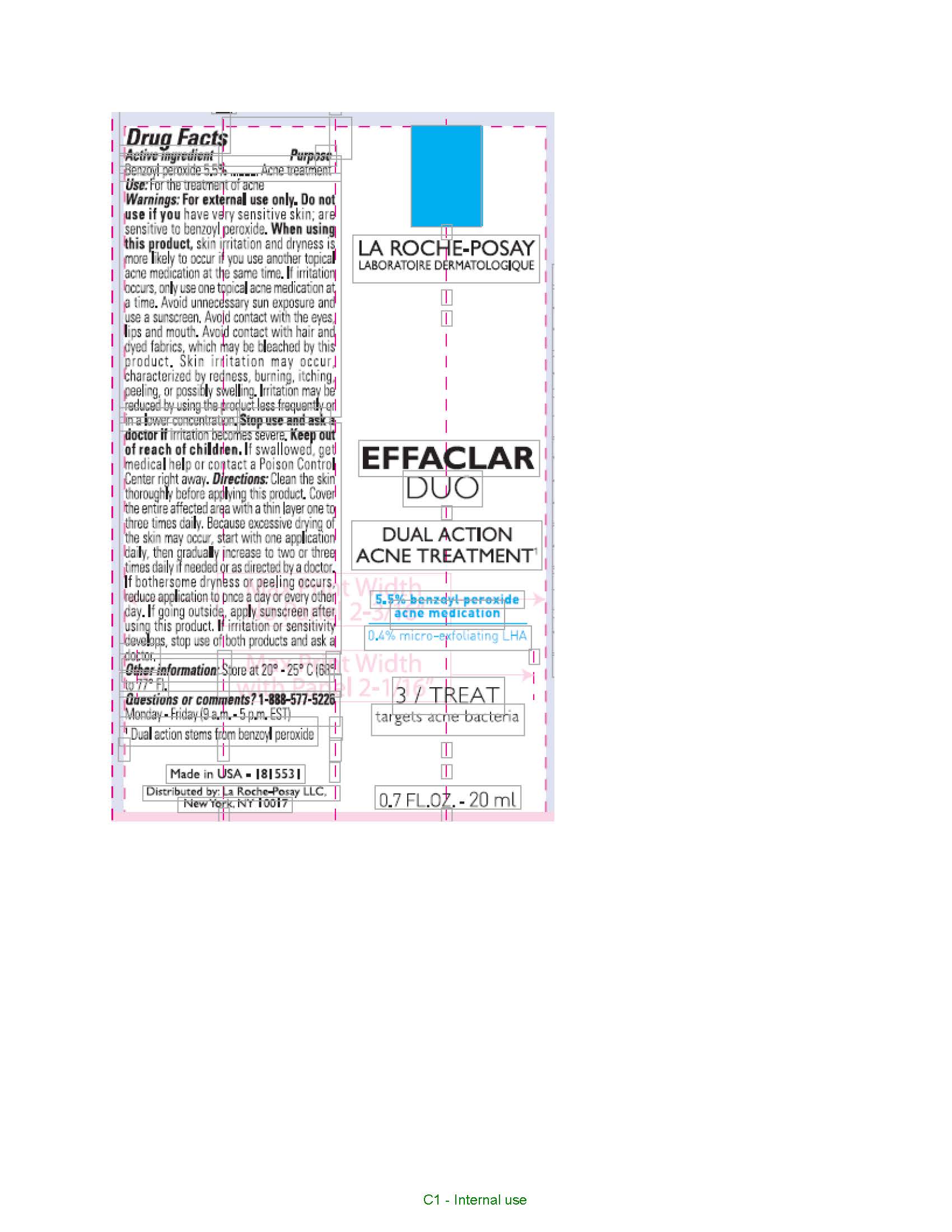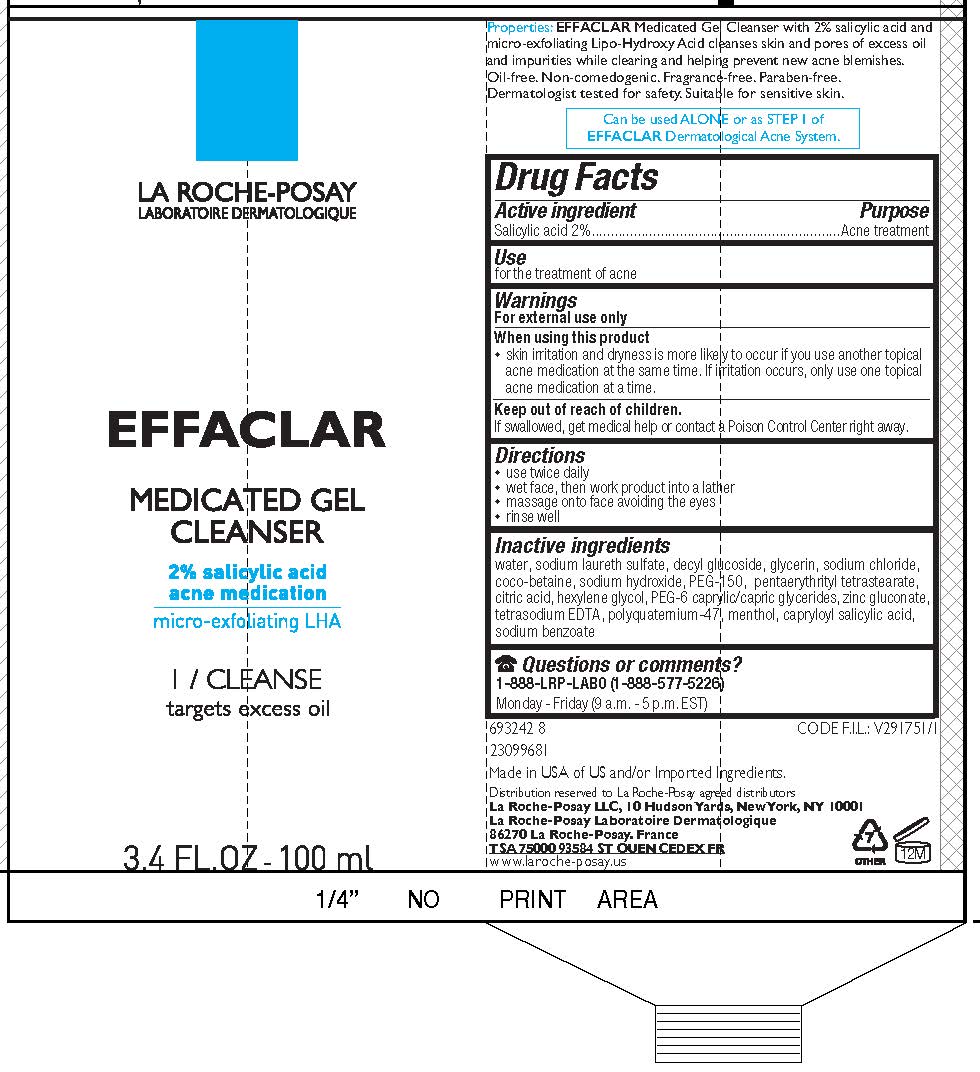 DRUG LABEL: La Roche Posay Effaclar Dermatological Acne System 3 Step Acne Routine
NDC: 49967-282 | Form: KIT | Route: TOPICAL
Manufacturer: L'Oreal USA Products Inc
Category: otc | Type: HUMAN OTC DRUG LABEL
Date: 20241021

ACTIVE INGREDIENTS: SALICYLIC ACID 20 mg/1 mL; SALICYLIC ACID 5 mg/1 mL; BENZOYL PEROXIDE 55 mg/1 mL
INACTIVE INGREDIENTS: WATER; SODIUM LAURETH SULFATE; DECYL GLUCOSIDE; GLYCERIN; SODIUM CHLORIDE; COCO-BETAINE; SODIUM HYDROXIDE; PEG-150 PENTAERYTHRITYL TETRASTEARATE; CITRIC ACID MONOHYDRATE; HEXYLENE GLYCOL; PEG-6 CAPRYLIC/CAPRIC GLYCERIDES; ZINC GLUCONATE; EDETATE SODIUM; POLYQUATERNIUM-47 (METHACRYLAMIDOPROPYLTRIMETHYLAMMONIUM CHLORIDE-CO-METHYL ACRYLATE-CO-ACRYLIC ACID 46:8:46; 1300000 MW); MENTHOL; CAPRYLOYL SALICYLIC ACID; SODIUM BENZOATE; WATER; ALCOHOL; PROPANEDIOL; GLYCOLIC ACID; SODIUM HYDROXIDE; CAPRYLOYL GLYCINE; PHENOXYETHANOL; BENZYL ALCOHOL; PPG-26-BUTETH-26; MENTHOL; BUTYLENE GLYCOL; WATER; ISOSTEARYL ALCOHOL; GLYCERIN; PENTYLENE GLYCOL; SILICA; CARBOMER; CAPRYLOYL SALICYLIC ACID; POTASSIUM HYDROXIDE; ACRYLATES/C10-30 ALKYL ACRYLATE CROSSPOLYMER (60000 MPA.S AT 0.5%); EDETATE DISODIUM; EPILOBIUM ANGUSTIFOLIUM FLOWER/LEAF/STEM EXTRACT

Drug Facts

Effaclar Medicated Gel Cleanser

Drug Facts

Active ingredient

Salicylic acid 2%

Purpose

Acne treatment

Use

for the treatment of acne

Warnings

For external use only

When using this product

- skin irritation and dryness is more liekly to occur if you use another topical acne medication at the same time. If irritation occurs, only use one topical acne medication at a time.

Keep out of reach of children.

If swallowed, get medical help or contact a Poison Control Center right away.

Directions

- use twice daily
- wet face, then work product into a lather
- massage onto face avoiding the eyes
- rinse well

Inactive Ingredients

water, sodium laureth sulfate, decyl glucoside, glycerin, sodium chloride, coco-betaine, sodium hydroxide, PEG-150 pentaerythrityl tetrastearate, citric acid, hexylene glycol, PEG-6 caprylic/capric glycerides, zinc gluconate, tetrasodium EDTA, polyquaternium-47, menthol, capryloyl salicylic acid, sodium benzoate

Questions or comments?

1-888-577-5226

Monday - Friday (9 a.m. - 5 p.m. EST)

Effaclar Clarifying Solution

Drug Facts

Active ingredient

Salicylic acid 0.5%

Purpose

Acne treatment

Use

for the treatment of acne

Warnings

For external use only

When using this product

skin irritation and dryness is more likely to occur if you use another topical acne medication at the same time. If irritation occurs, only use one topical acne medication at a time.

Keep out of reach of children.

If swallowed, get medical help or contact a Poison Control Center right away.

Directions

- clean the skin thoroughly before applying this product
- cover the entire affected area with a thin layer one to three times daily
- because excessive drying of the skin may occur, start with one application daily, then gradually increase to two or three times daily if needed or as directed by a doctor
- if bothersome dryness or peeling occurs, reduce application to once a day or every other day

Other information

Sunburn Alert: This product contains an alpha hydroxy acid (AHA) that may increase your skin's sensitivity to the sun and particularly the possibility of sunburn. Use a sunscreen, wear protective clothing and limit sun exposure while using this product and for a week afterwards.

Inactive Ingredients

water, alcohol denat., propanediol, glycolic acid, sodium hydroxide, capryloyl glycine, phenoxyethanol, benzyl alcohol, PPG-26-buteth-26, PEG-40 hydrogenated castor oil, menthol, tremella fuciformis polysaccharide, butylene glycol, ophiopogon japonicus root extract, scutellaria baicalensis root extract

Questions or comments?

1-888-577-5626

Effaclar Duo Dual Action Acne Treatment

Drug Facts

Active ingredient

Benzoyl peroxide 5.5%

Purpose

Acne medication

Uses

- for the treatment of acne
- dries and clears acne blemishes and allows skin to heal

Warnings

For external use only

Do not use if you

- have very sensitive skin
- are sensitive to benzoyl peroxide

When using this product

- skin irritation and dryness is more likely to occur if you use another topical acne medication at the same time. If irritation occurs, only use one topical acne medication at a time.
- avoid unnecessary sun exposure and use a sunscreen
- avoid contact with the eyes, lips, and mouth
- avoid contact with hair and dyed fabrics, which may be bleached by this product
- skin irritation may occur, characterized by redness, burning, itching, peeling, or possibly swelling. Irritation may be reduced by using the product less frequently or in a lower concentration

Stop use and ask a doctor if

irritation becomes severe

Keep out of reach of children.

If swallowed, get medical help or contact a Poison Control Center right away.

Directions

- cleanse the skin thoroughly before applying this product
- cover the entire affected area with a thin layer one to three times daily
- because excessive drying of the skin may occur, start with one application daily, then gradually increase to two or three times daily if needed or as directed by a doctor
- if bothersome dryness or peeling occurs, reduce application to once a day or every other day
- if going outside, apply sunscreen after using this product. If irritation or sensitivity develops, stop use of both products and ask a doctor.

Other information

store at 20° - 25°C (68° - 77°F)

Ingredients

water, isostearyl alcohol, glycerin, pentylene glycol, silica, carbomer, capryloyl salicylic acid, potassium hydroxide, tocopheryl acetate, acrylates/C10-30 alkyl acrylate crosspolymer, disodium EDTA, epilobium angustifolium flower/leaf/stem extract

Questions or comments?

1-888-LRP-LABO 1-888-577-5226

Monday - Friday (9 a.m. - 5 p.m. EST)